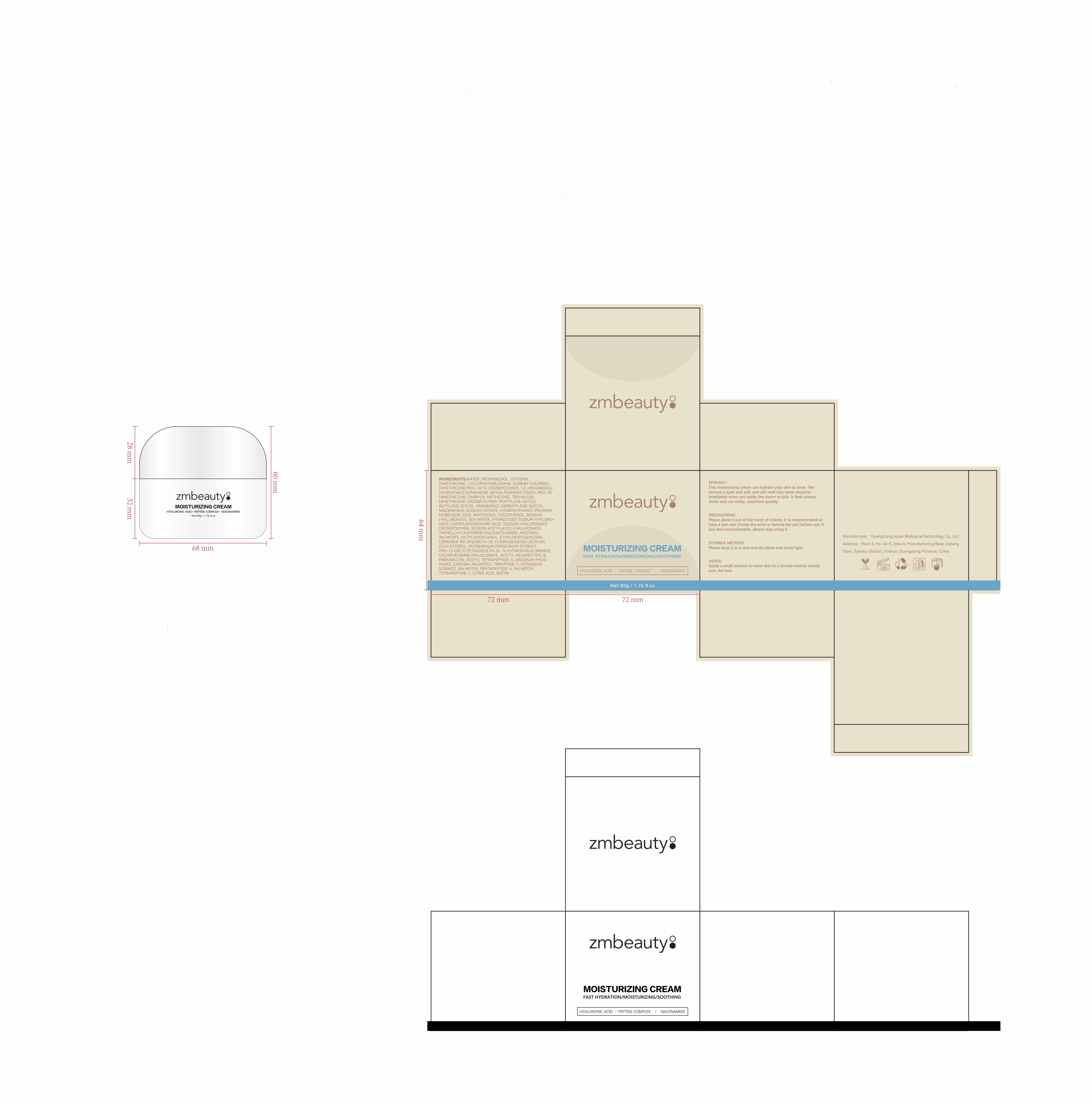 DRUG LABEL: baoshishuang
NDC: 84716-898 | Form: EMULSION
Manufacturer: Shenzhen Boyang E-commerce Co.
Category: otc | Type: HUMAN OTC DRUG LABEL
Date: 20240926

ACTIVE INGREDIENTS: PROPANEDIOL 5.00195 g/50 g; GLYCERIN 4.000925 g/50 g; DIMETHICONE 2.6292 g/50 g
INACTIVE INGREDIENTS: WATER 33.4263 g/50 g

ACTIVE INGREDIENTS

PROPANEDIOL 10.0039%

GLYCERIN 8.00185%

DIMETHICONE 5.2584%

PURPOSE

HYALURONIC ACID,PEPTDE COMPLEX,NIACINAMIDE

usege

Apply a small amount to clean skin in a circular motion evenly over the face.

Warnings

Please place it out of the reach of infants;

lt is recommended to have a skin test (inside the wrist or behind the ear) before use.

lf you feel uncomfortable,please stop using it.

Stop use and ask a doctor if

lt is recommended to have a skin test (inside the wrist orbehind the ear) before use.If you feel uncomfortable,please stop using it.

Do not use

on damaged or broken skin

Keep out of reach of children

Please place it out of the reach of infants；If swallowed, get medical help or contact a Poison Control Center right away.

When using this product

FOR EXTERNAL USE ONIY

keep out of eyes. Rinse with water to remove.

uses and storage method

STORAGE METHOD:

Please keep it in a cool and dry place and avoid light.
USAGE:

Apply a small amount to clean skin in a circular motion evenly over the face.

INACTIVE INGREDIENT SECTON

WATER,SODIUM CHLORIDE,FRAGRANCE,CAPRYLHYDROXAMIC ACID,STEARETH-20,POTASSIUM SORBATE,CITRIC ACID,SEA WATER